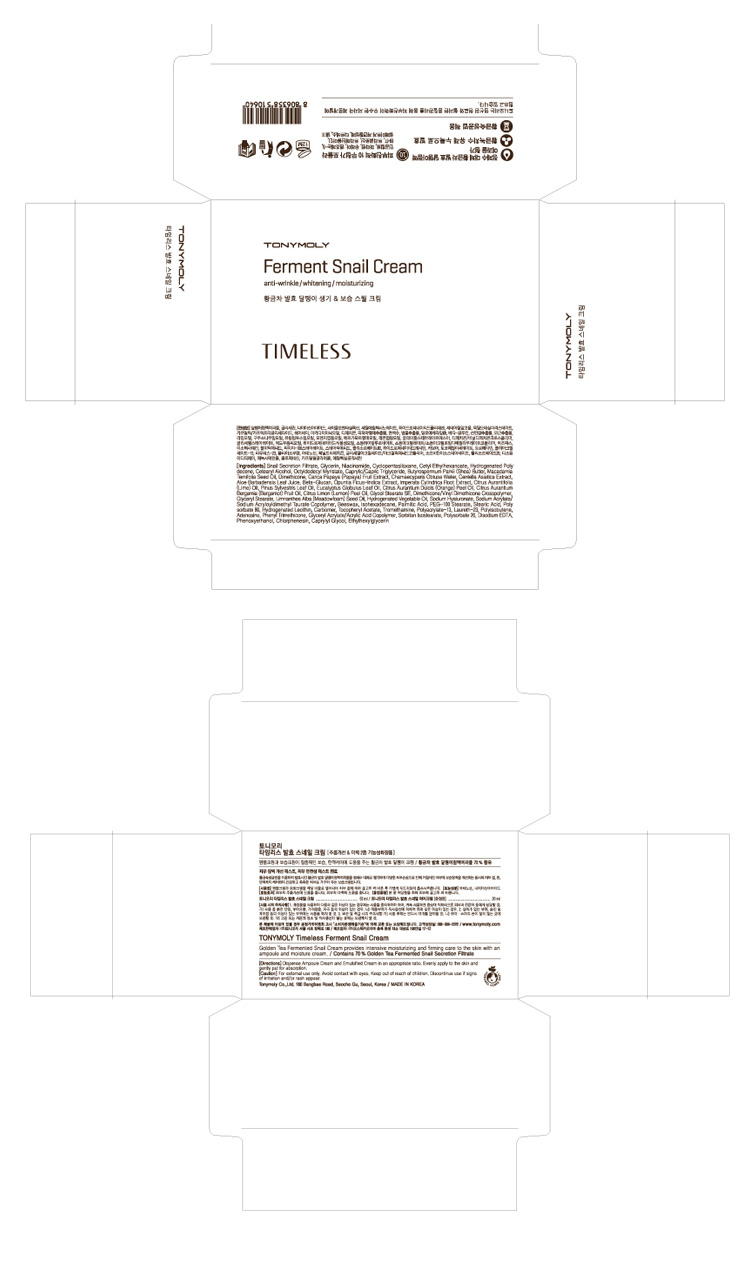 DRUG LABEL: TONYMOLY Timeless Ferment Snail Cream
NDC: 59078-103 | Form: CREAM
Manufacturer: Tonymoly Co., Ltd.
Category: otc | Type: HUMAN OTC DRUG LABEL
Date: 20160202

ACTIVE INGREDIENTS: GLYCERIN 4910.1 mg/50 mL
INACTIVE INGREDIENTS: GLYCERYL MONOSTEARATE; MEADOWFOAM SEED OIL; LEMON PEEL; EDETATE DISODIUM; BERGAMOT OIL; GLYCIDYL ACRYLATE; ORANGE PEEL; CHAMAECYPARIS OBTUSA WHOLE; LIME OIL; PINE NEEDLE OIL (PINUS SYLVESTRIS); IMPERATA CYLINDRICA ROOT; HYALURONATE SODIUM; EUCALYPTUS GLOBULUS LEAF; PAPAYA; CETYL ETHYLHEXANOATE; BUTYLENE GLYCOL; HYDROGENATED POLYDECENE (550 MW); OCTYLDODECYL MYRISTATE; DIMETHICONE; POLYSORBATE 80; ETHYLHEXYLGLYCERIN; CAPRYLYL GLYCOL; LAURETH-23; ADENOSINE; SORBITAN ISOSTEARATE; POLYSORBATE 20; PROPANEDIOL; NIACINAMIDE; SODIUM BENZOATE; WATER; PEG-100 STEARATE; ISOHEXADECANE; PALMITIC ACID; PHENOXYETHANOL; CHLORPHENESIN; STEARIC ACID; SHEA BUTTER; GLYCERYL STEARATE SE; DIMETHICONE/VINYL DIMETHICONE CROSSPOLYMER (HARD PARTICLE); SODIUM ACRYLATE; YELLOW WAX; HYDROGENATED SOYBEAN LECITHIN; OPUNTIA FICUS-INDICA; POLYETHYLENE GLYCOL 400; CENTELLA ASIATICA; ALOE VERA LEAF

Active Ingredients

Glycerin 7.79415%

Purpose

Skin Protectant

Dosage

Apply a small amount of this product.

Caution

For external use only. Avoid contact with eyes. Keep out of reach of children. Discontinue use if signs of irritation and/or rash appear.

Keep out of reach of children. Discontinue use if signs of irritation and/or rash appear.

Directions

Dispense Ampoule Cream and Emulsified Cream in an appropriate ratio. Evenly apply to the skin and gently pat for absorption.

After essence, apply evenly across the face.

Inactive Ingredients

Octyldodecyl Myristate, Macadamia Ternifolia Seed Oil, Caprylic/Capric Triglyceride, Butyrospermum Parkii (Shea) Butter, Dimethicone, Glycol Stearate SE, Dimethicone/Vinyl Dimethicone Crosspolymer, Glyceryl Stearate, Limnanthes Alba (Meadowfoam) Seed Oil, Hydrogenated Vegetable Oil, Sodium Acrylate/Sodium Acryloyldimethyl Taurate Copolymer, Water, PEG-100 Stearate, Isohexadecane, Beeswax, Palmitic Acid, Phenoxyethanol, Carbomer, Polysorbate 80, Chlorphenesin, Stearic Acid, Hydrogenated Lecithin, Tromethamine, Polyacrylate-13, Ethylhexylglycerin, Caprylyl Glycol, Tocopheryl Acetate, Polyisobutene, Laureth-23, Citrus Limon (Lemon) Peel Oil, Adenosine, Phenyl Trimethicone, Disodium EDTA, Citrus Aurantium Bergamia (Bergamot) Fruit Oil, Alcohol, Sorbitan Isostearate, Polysorbate 20, Citrus aurantium dulcis (orange) peel oil, Glyceryl Acrylate/Acrylic Acid Copolymer, Chamaecyparis Obtusa Water, Citrus Aurantifolia (Lime) Oil, Pinus Sylvestris Leaf Oil, Imperata Cylindrica Root Extract, Sodium Hyaluronate, Opuntia Ficus-Indica Extract, Eucalyptus Globulus Leaf Oil, Propanediol, PEG-8, Centella Asiatica Extract, Carica papaya (papaya) fruit Extract, Aloe Barbadensis Leaf Juice, Beta-Glucan, Citric Acid, Potassium sorbate, Sodium Benzoate